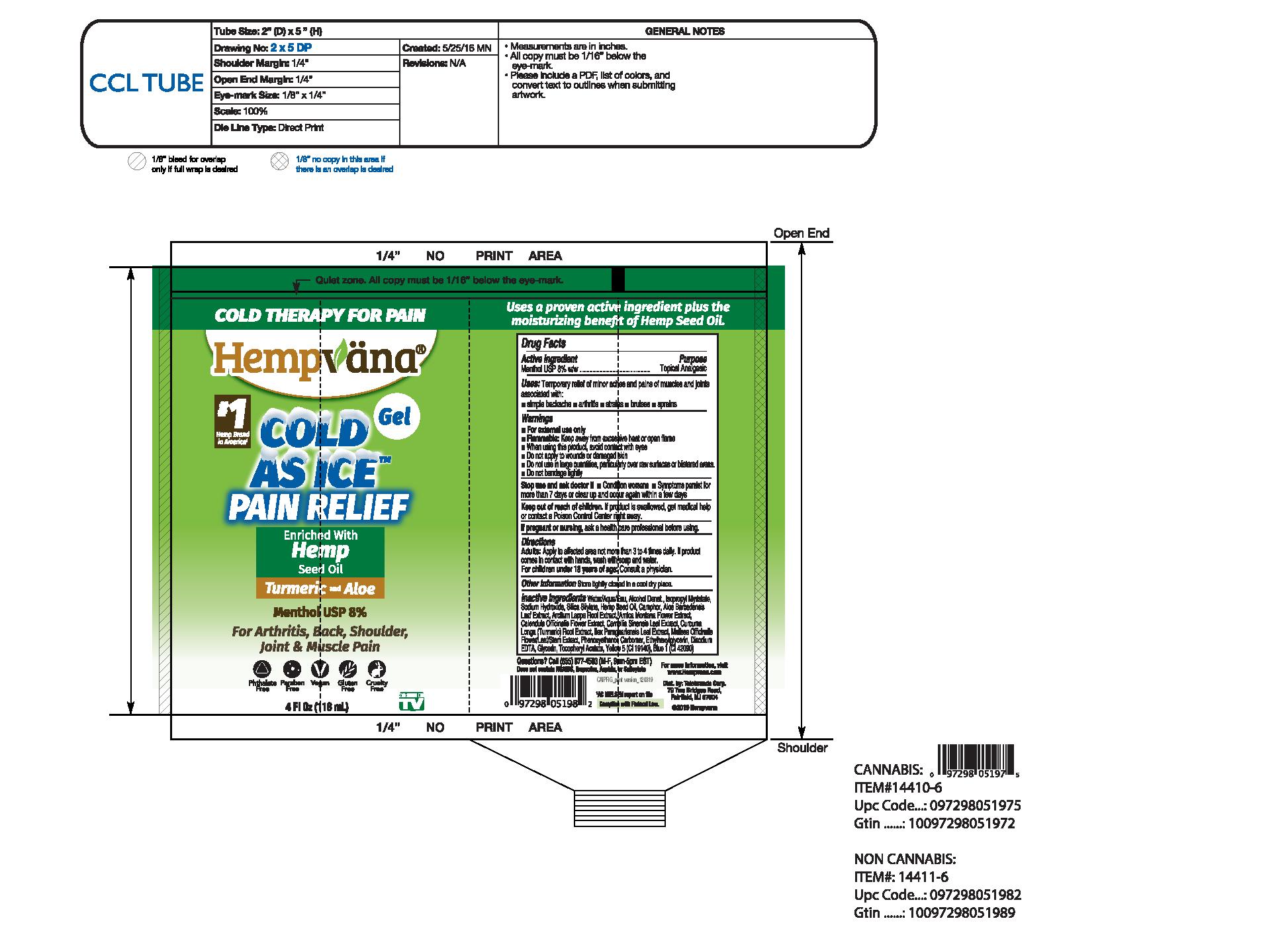 DRUG LABEL: Hempvana Cold as Ice Gel
NDC: 73287-012 | Form: GEL
Manufacturer: Telebrands Corp
Category: otc | Type: HUMAN OTC DRUG LABEL
Date: 20241120

ACTIVE INGREDIENTS: MENTHOL 8 mg/100 mL
INACTIVE INGREDIENTS: ISOPROPYL MYRISTATE; SODIUM HYDROXIDE; WATER; CAMPHOR, (-)-; TURMERIC; CARBOMER HOMOPOLYMER, UNSPECIFIED TYPE; ALPHA-TOCOPHEROL ACETATE; GREEN TEA LEAF; MELISSA OFFICINALIS FLOWERING TOP; EDETATE DISODIUM; FD&C BLUE NO. 1; ALCOHOL; SILICA DIMETHYL SILYLATE; ILEX PARAGUARIENSIS LEAF; PHENOXYETHANOL; ETHYLHEXYLGLYCERIN; FD&C YELLOW NO. 5; GLYCERIN; CANNABIS SATIVA SEED OIL; ALOE VERA LEAF; ARCTIUM LAPPA ROOT; ARNICA MONTANA FLOWER; CALENDULA OFFICINALIS FLOWERING TOP

Hempvana Cold As Ice Gel

Active Ingredient

Menthol USP 8% w/w

Purpose

Menthol USP 8% w/w................Topical Analgesic

Uses

temporarily relief of minor aches and pains of muscles and joints associated with:

• simple backache • arthritis • strains • bruises • sprains

WARNINGS

For external use only

Flammable: Keep away from excessive heat or open flame

When using this product, avoid contact with eyes.

- Do not apply to wounds or damaged skin
- Do nut use in large quantities, particularly over raw surfaces or blistered areas.
- Do not bandage tightly

Stop use and ask a doctor if

- Condition worsens
- Symptoms persist for more than 7 days or clear up and occur again within a few days

Keep out of reach of children. If product is swallowed, get medical help or contact a Poison Control Center right away.

PREGNANCY OR BREAST FEEDING

If pregnant or nursing,ask a healthcare professional before using.

Directions

Adults:Apply to affected are not more than 3 to 4 times daily. If product comes in contact with hands, wash with soap and water.

For children under 18 years of age: Consult a physician.

Other Information

Store tightly closed in a cool dry place.

Inactive Ingredients

water/aqua/eau, alcohol denat., isopropyl myristate, sodium hydroxide, silica silylate, hemp seed oil, camphor, aloe barbadensis leaf extract, arctium lappa root extract, arnica montana flower extract, calendula officinalis flower extract, camellia sinensis leaf extract, curcuma longa (turmeric) root extract, ilex paraguariensis leaf extract, melissa officinalis flower/leaf/stem extract, phenoxyethanol, carbomer, ethylhexylglycerin, disodium edta, tocopheryl acetate, Yellow 5 (Cl 19140), Blue 1 (Cl 42090).

DESCRIPTION

Call (855) 877-4503 (M-F, 9am-5pm EST)

Does not contain NSAIDS, ibuprofen, Aspirin or Salicylate

For more information visit www.hempvana.com

Dist. By: Telebrands Corp.

79 Two Bridges Road

Fairfield, NJ 07004

PACKAGE LABEL

Cold Therapy For Pain

Hempvana

#1 Hemp Brand in America

Cold as Ice Pain Relief Gel

Enriched with hemp seed oil turmeric and aloe

Menthol USP 8%

For arthritis, back, shoulder, joint & muscle pain

phthalate free - paraben free - vegan - gluten free - cruelty free

4 fl oz (118 mL)

As seen on TV